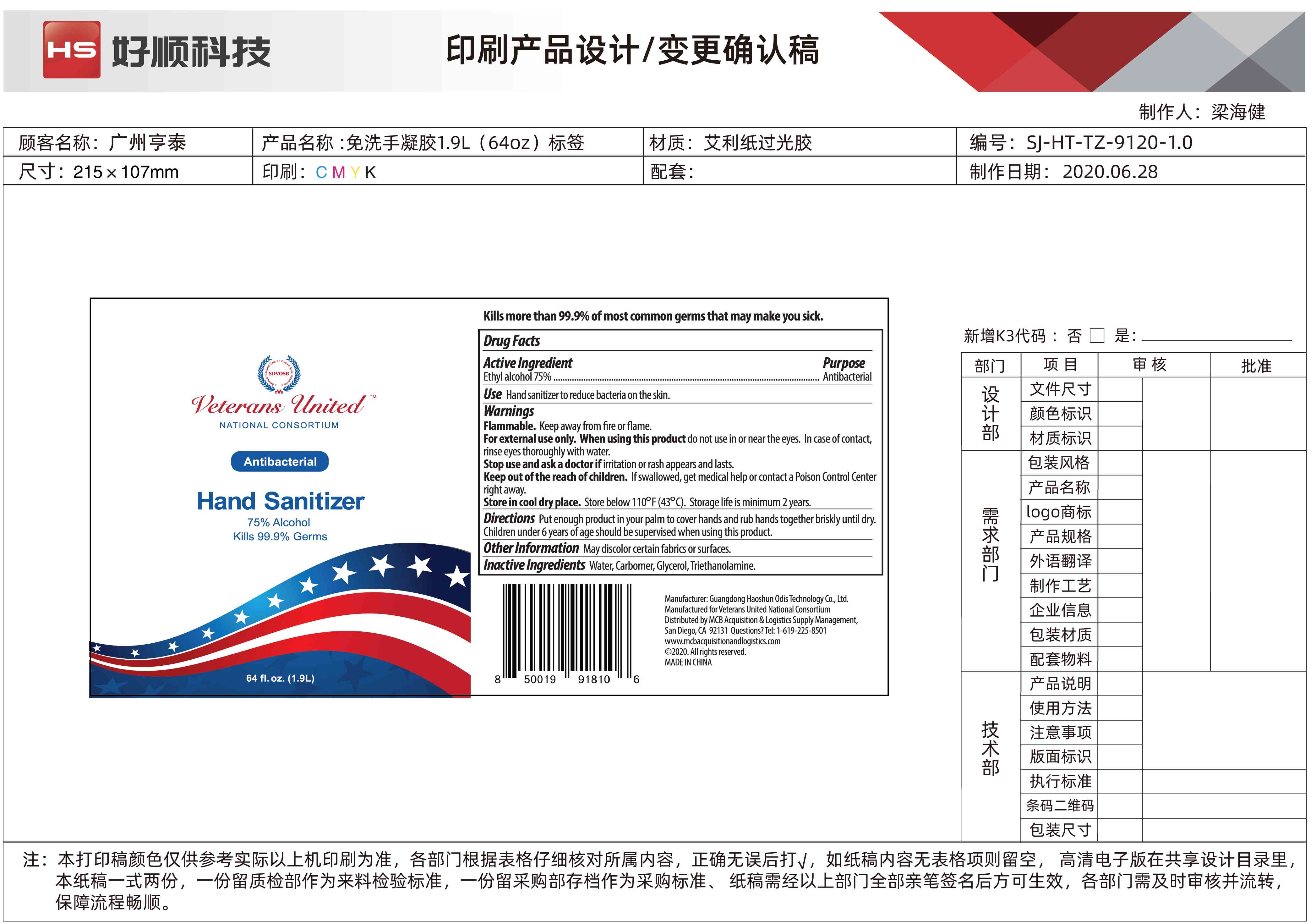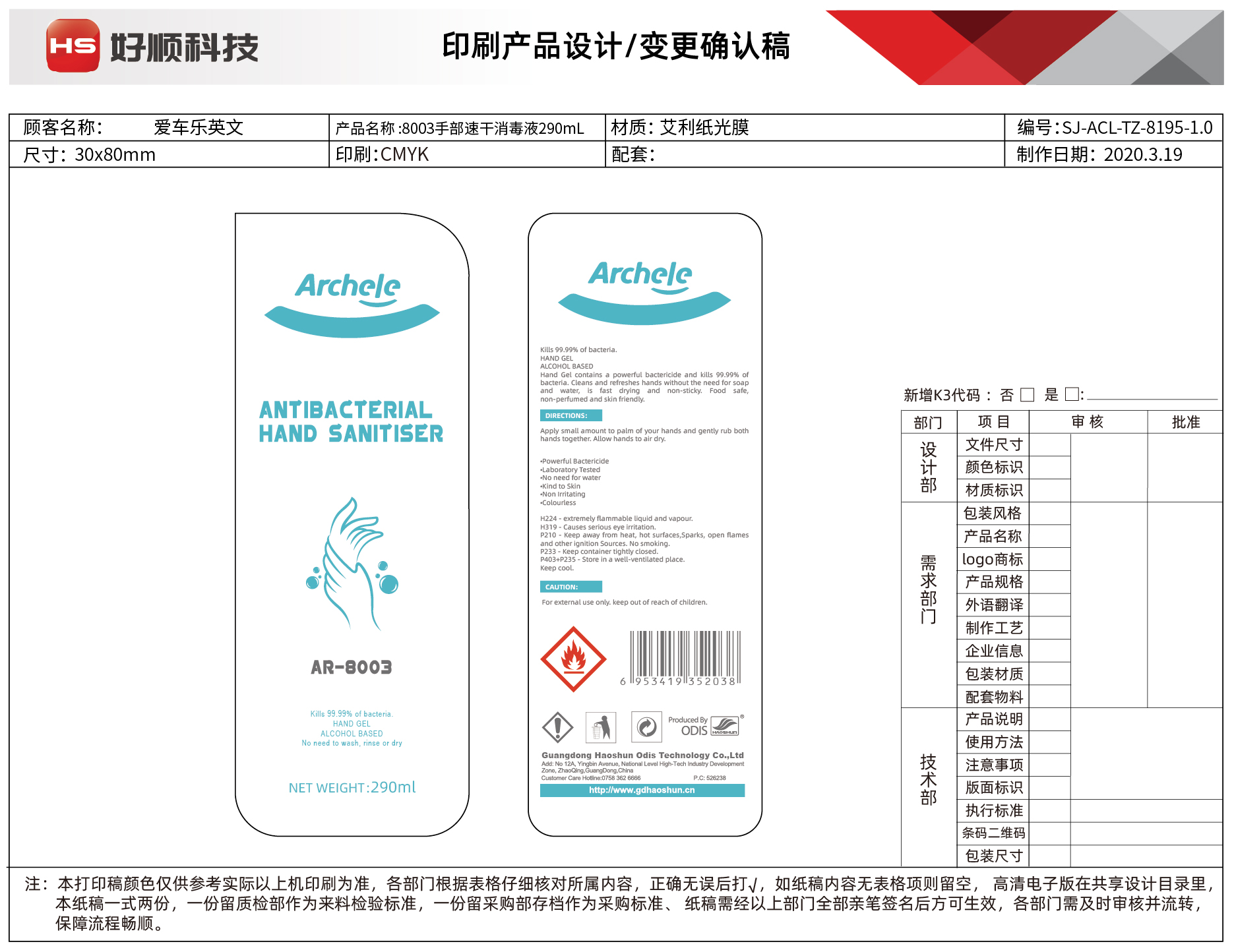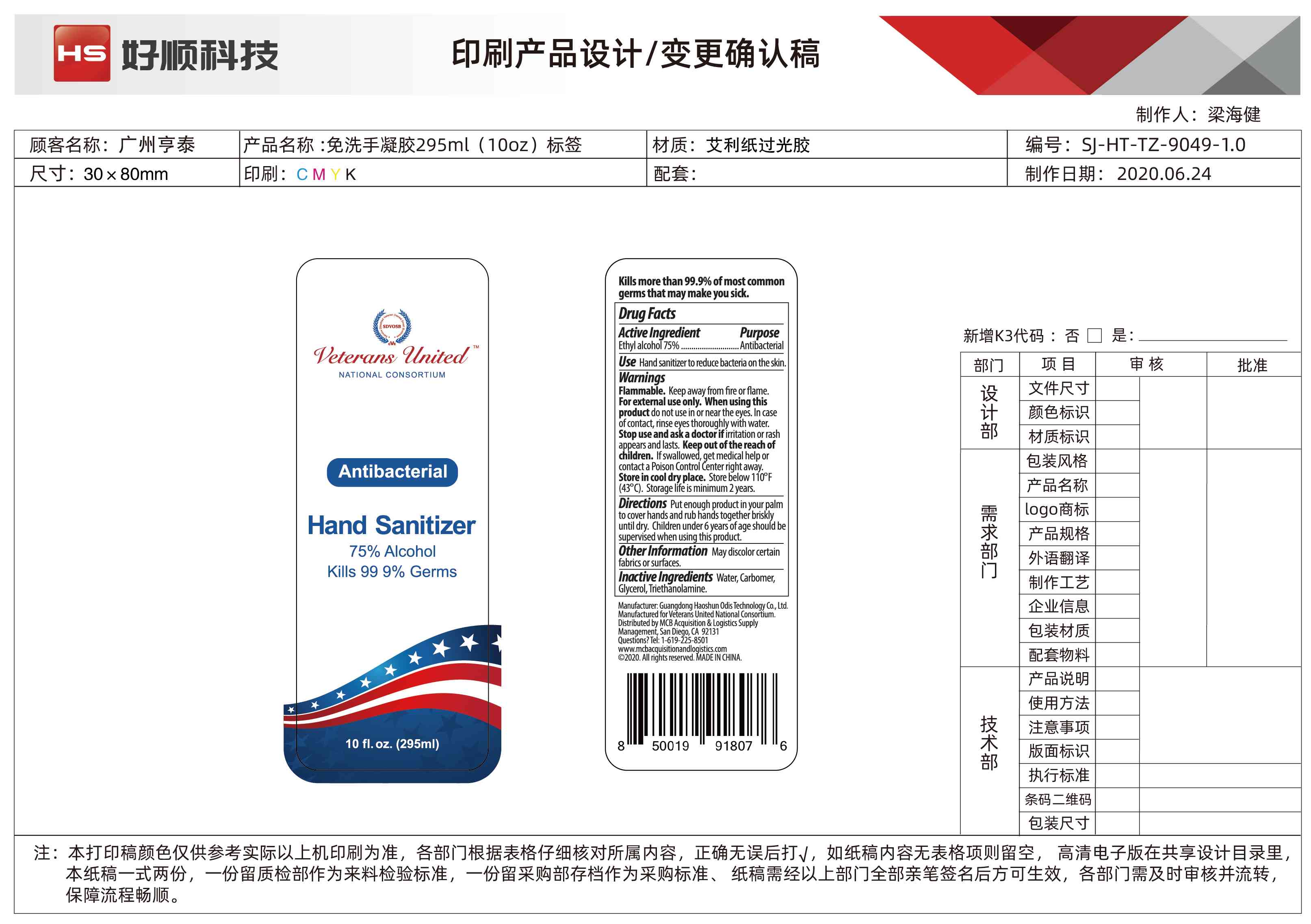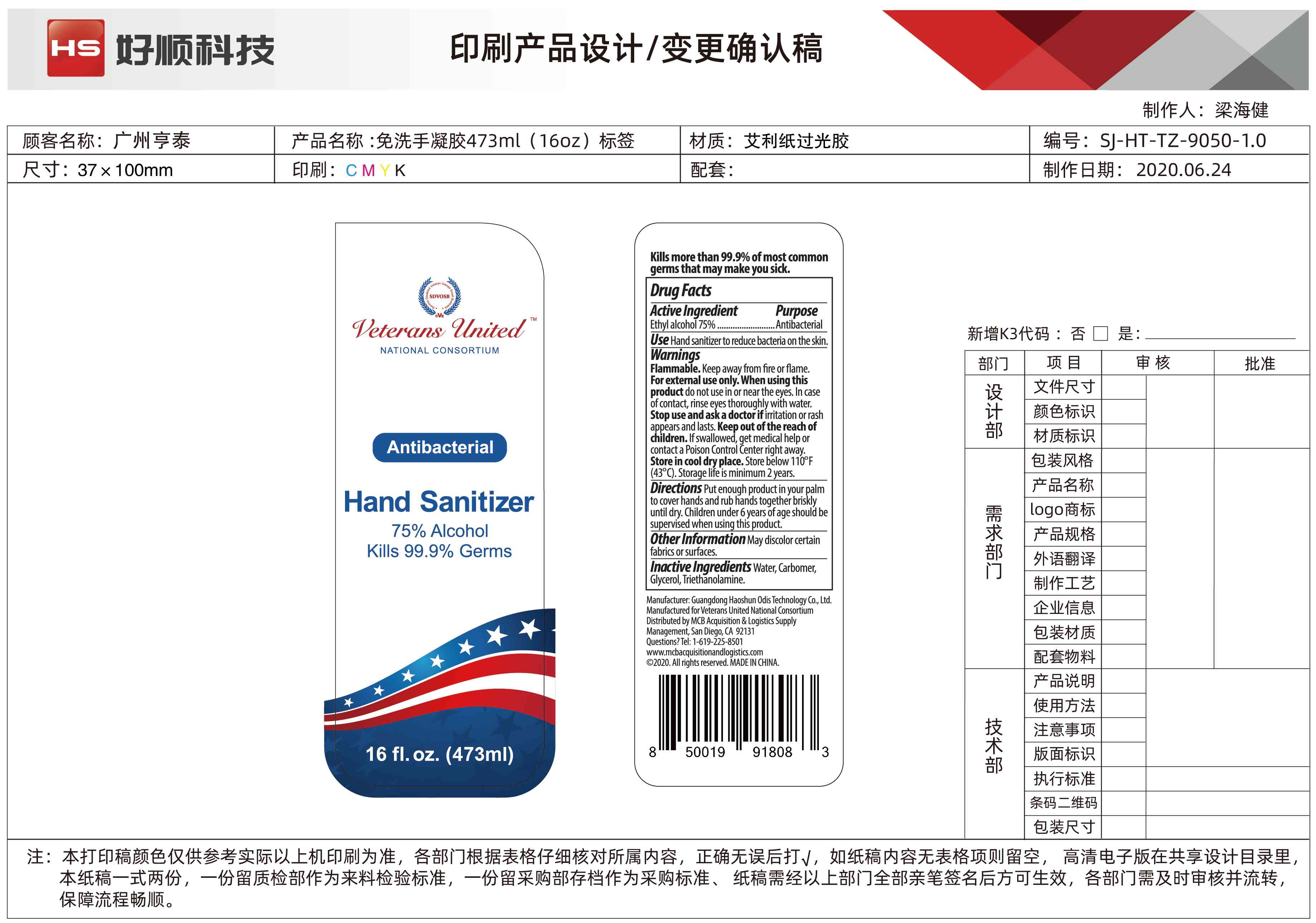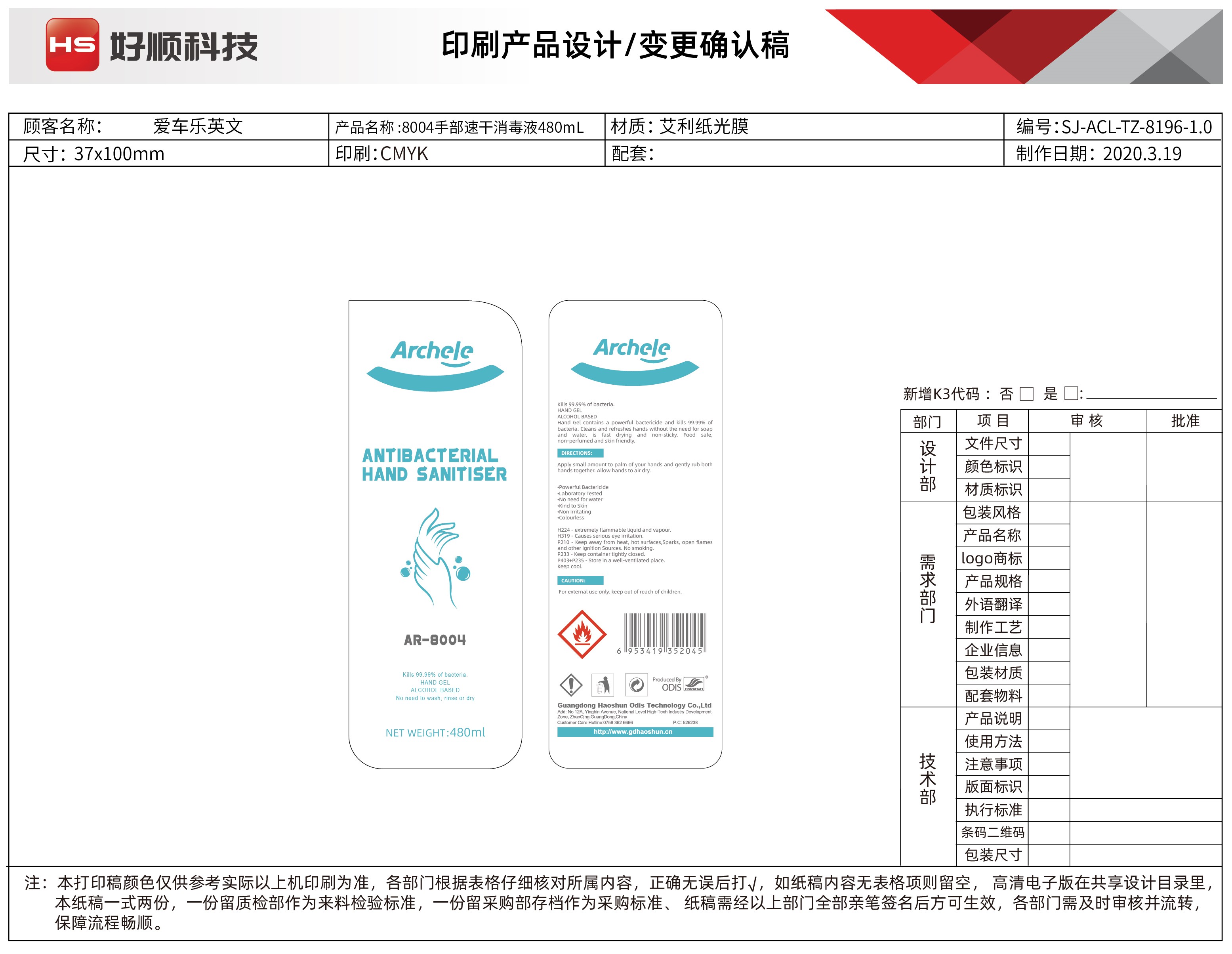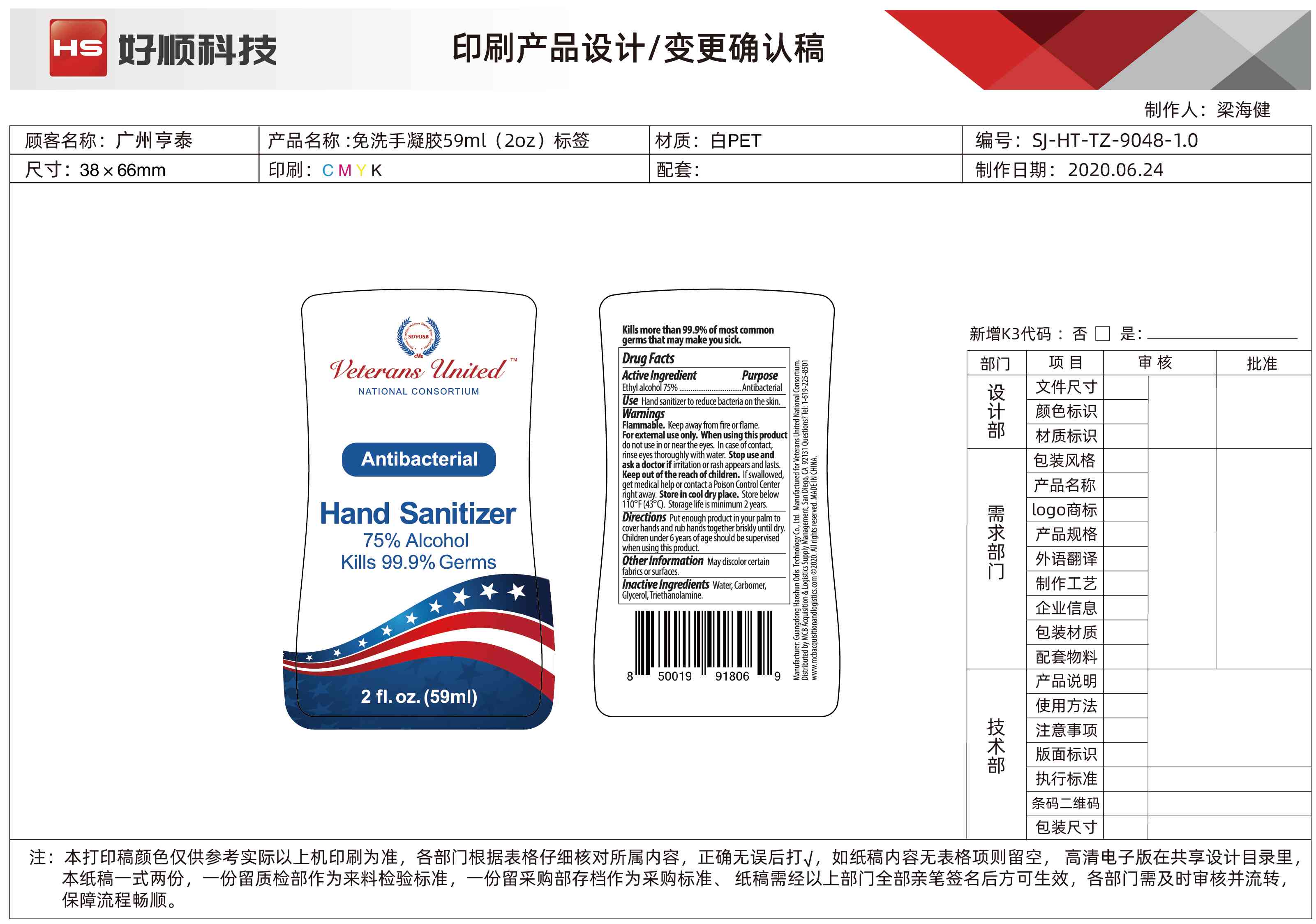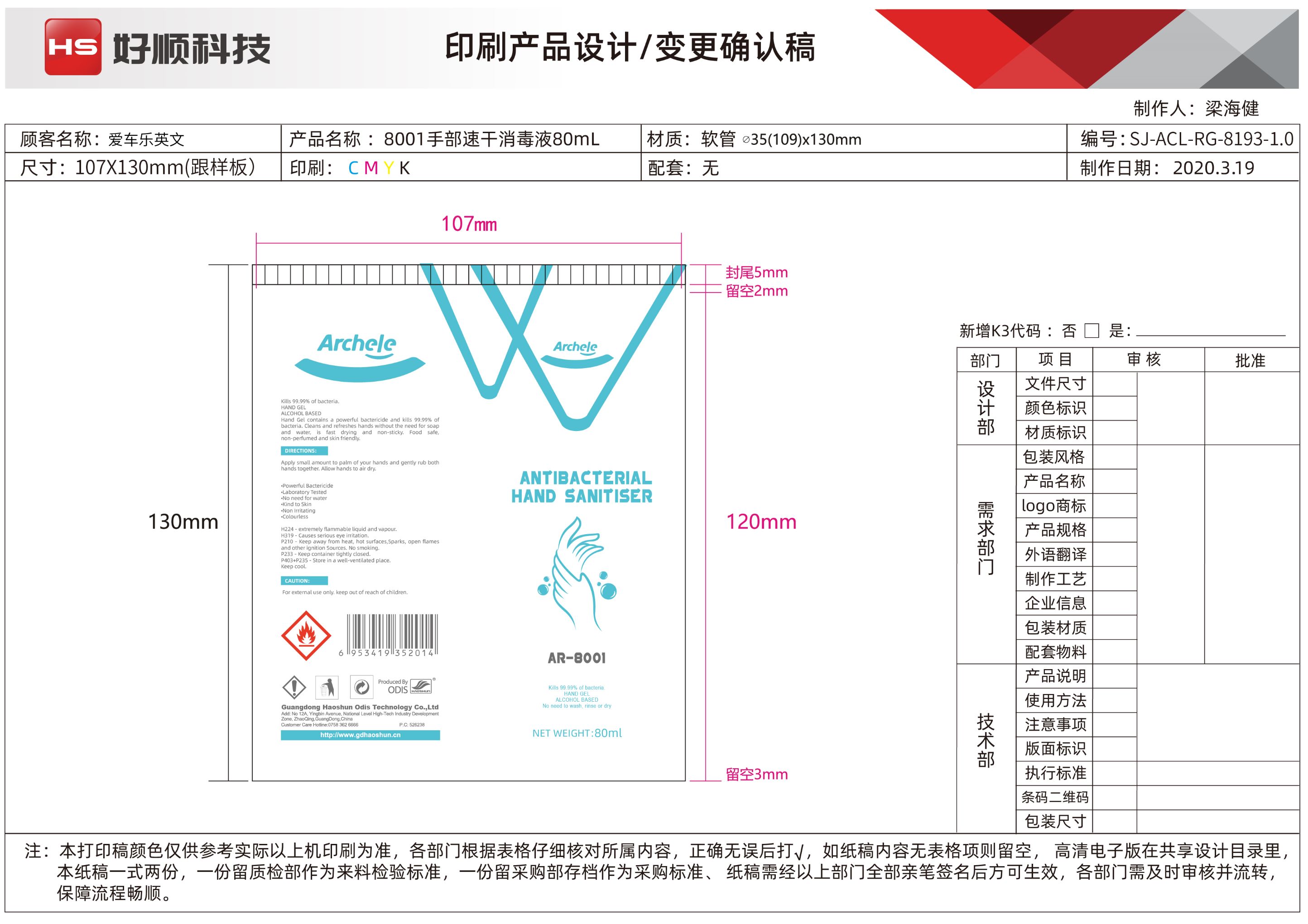 DRUG LABEL: Hand Sanitizer
NDC: 74895-103 | Form: GEL
Manufacturer: GUANGDONG HAOSHUN ODIS TECHNOLOGY COMPANY LIMITED
Category: otc | Type: HUMAN OTC DRUG LABEL
Date: 20210111

ACTIVE INGREDIENTS: ALCOHOL 75 mL/100 mL
INACTIVE INGREDIENTS: CARBOMER HOMOPOLYMER, UNSPECIFIED TYPE 0.35 mL/100 mL; TROLAMINE 0.12 mL/100 mL; WATER; GLYCERIN 0.5 mL/100 mL; BETAINE 0.25 mL/100 mL

Archele & Veterans United Hand Sanitizer

Information -

This is a hand sanitizer manufactured according to the Temporary Policy for Preparation of Certain Alcohol-Based Hand Sanitizer Products During the Public Health Emergency (CoViD-19); Guidance for Industry.

The hand sanitizer is manufactured using only the following United States Pharmacopoeia (USP) grade ingredients in the preparation of the product (percentage in final product formulation) consistent with World Health Organization (WHO) recommendations.

Active ingredient & Purpose

Antiseptic, Hand Sanitizer

Active ingredient | Purpose
Alcohol 75% v/v.................... | Antiseptic

Use

Hand Sanitizer to help reduce bacteria that potentially can cause disease. For use when soap and water are not available.

Warnings

For external use only. Flammable. Keep away from heat or flame

Do not use

- in children less than 2 months of age
- on open skin wounds

When using this product

- Keep out of eyes, ears, and mouth. In case of contact with eyes, rinse eyes thoroughly with water.

Stop use and ask a doctor if

irritation or rash occurs. These may be signs of a serious condition.

Keep out of reach of children.

If swallowed, get medical help or contact a Poison Control Center right away.

Directions

- Place enough product on hands to cover all surfaces. Rub hands together until dry.
- Supervise children under 6 years of age when using this product to avoid swallowing.

Other Information

- Store between 15-30C (59-86F)
- Avoid freezing and excessive heat above 40C (104F)

Inactive ingredients

glycerin, trolamine, betaine, carbomer homopolymer, purified water USP

Packaging Label

1.9L ml NDC: 74895-103-09

473 ml NDC: 74895-103-08

295 ml NDC: 74895-103-07

59 ml NDC: 74895-103-06

80 mL NDC: 74895-103-01

480 mL NDC: 74895-103-02

290 mL NDC: 74895-103-03